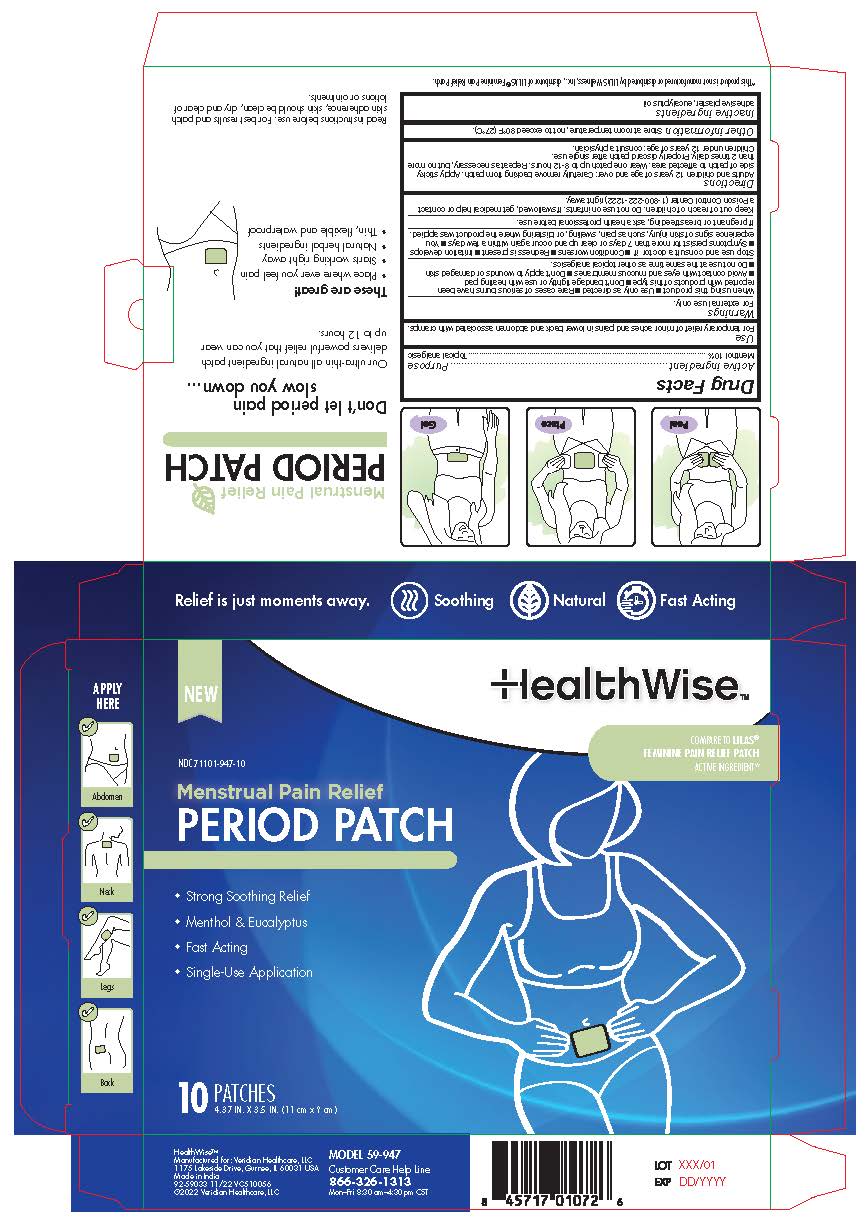 DRUG LABEL: HealthWise Menstrual Pain Relief Patch
NDC: 71101-947 | Form: PATCH
Manufacturer: Veridian Healthcare
Category: otc | Type: HUMAN OTC DRUG LABEL
Date: 20241218

ACTIVE INGREDIENTS: MENTHOL, UNSPECIFIED FORM 10 g/100 g
INACTIVE INGREDIENTS: EUCALYPTUS OIL

HealthWise Menstrual Pain Relief Patch

Active Ingredients (In each patch)

Menthol 10.0%

Purpose

Topical Analgesic

Uses

For temporary relief of minor aches and pains in lower back abdomen associated with cramps

Warnings

For external use only

Keep out of reach of children. If swallowed, get medical help or contact a Poison Control Center right away.

When using this product

- Use only as directed
- Rare cases of serious burns have been reported with products of this type
- Don't bandage tightly or use with heating pad
- Avoid contact with the eyes, mucous membranes
- Do not apply to wounds or damaged skin
- Do not use at the same time as other topical analgesics.

Stop using and consult a doctor if

- Condition worsens
- Redness is present
- Irritation develops
- Symptoms persist for more than 7 days or clear up and occur again within a few days
- You experience signs of skin injury, such as pain, swelling, or blistering where the product was applied.

If pregnant or breastfeeding

as a health professional before use

Keep out of reach of children

Do not use on infants. If swallowed, get medical help or contact a Poison Control Center (1-800-222-1222) right away

Directions

Adults and children 12 years of age and over: Carefully remove backing from patch. Apply sticky side of patch to affected area. Wear one patch up to 8-12 hours. Repeat as necessary, but no more than 2 times daily. Properly discard patch after single use. children under 12 years of age consult a physician.

Other Information

Store at room temperature, not to exceed 80°F (27ºC)

Inactive Ingredients

• adhesive plaster • eucalyptus oil

Questions?

Call 1-866-326-1313